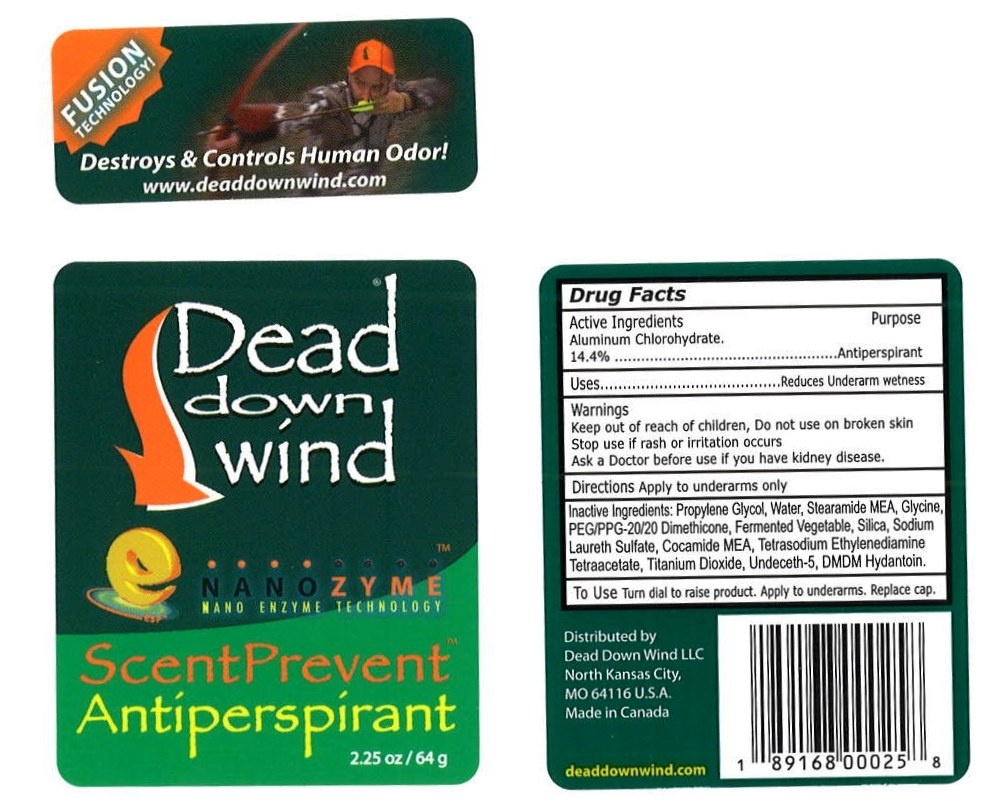 DRUG LABEL: Dead Down Wind ScentPrevent
NDC: 10889-103 | Form: STICK
Manufacturer: VVF Kansas Services LLC
Category: otc | Type: HUMAN OTC DRUG LABEL
Date: 20091029

ACTIVE INGREDIENTS: aluminum chlorohydrate 14.4 1/1 1

Dead Down Wind Scent Prevent (Aluminum Chlorohydrate)

ACTIVE INGREDIENT

Aluminum Chlorohydrate 14.4%

PURPOSE

Anti-Perspirant

USES

Reduces underarm wetness.

To Use Turn dial to raise product. Apply to underarms. Replace cap.

WARNINGS

Keep out of reach of children, Do not use on broken skin.

Stop use if rash or irritation occurs.

Ask a Doctor before use if you have kidney disease.

INACTIVE INGREDIENTS

Propylene Glycol, Water, Steramide MEA, Glycine, PEG/PPG-20/20 Dimethicone, Fermented Vegetable, Silica, Sodium Laureth Sulfate, Cocamide MEA, Tetrasodium Ethylenediamine Tetraacetate, Titanium Dioxide, Undeceth-5, DMDM Hydantoin.

Distributed by:
Dead Down Wind LLc
North Kansas City,
MO 64116 U.S.A.
Made in USA
deaddownwind.com

PRODUCT PACKAGING

FUSION TECHNOLOGY!

Destroys and Controls Human Odor!

www.deaddownwind.com

Dead down wind
NANOZYME (TM)
NANO ENZYME TECHNOLOGY
ScentPrevent
Antiperspirant
NDC 10889-103-12
2.25 oz / 64 g